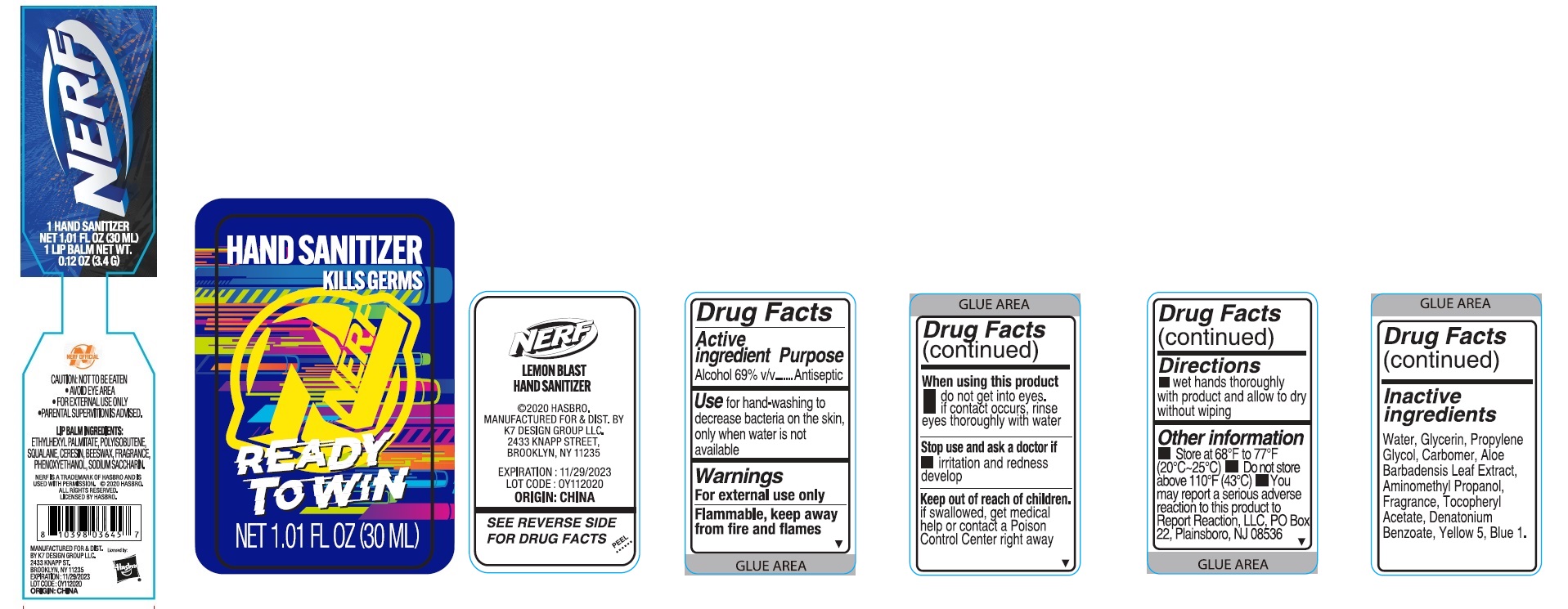 DRUG LABEL: Nerf Lemon Blast Hand Sanitizer and Lip Balm
NDC: 74177-972 | Form: KIT | Route: TOPICAL
Manufacturer: K7 Design Group Inc.
Category: otc | Type: HUMAN OTC DRUG LABEL
Date: 20201214

ACTIVE INGREDIENTS: ALCOHOL 69 mL/100 mL
INACTIVE INGREDIENTS: WATER; .ALPHA.-TOCOPHEROL ACETATE; GLYCERIN; ALOE VERA LEAF; DENATONIUM BENZOATE; FD&C BLUE NO. 1; PROPYLENE GLYCOL; CARBOMER HOMOPOLYMER, UNSPECIFIED TYPE; AMINOMETHYLPROPANOL; FD&C YELLOW NO. 5

Nerf Lemon Blast Hand Sanitizer and Lip Balm Kit

Active ingredient

Alcohol 69% v/v

Purpose

Antiseptic

Use

for hand-washing to decrease bacteria on the skin, only when water is not available

Warnings

For external use only

Flammable, keep away from fire and flames

When using this product

- do not get into eyes.
- if contact occurs, rinse eyes thoroughly with water

Stop use and ask a doctor if

- irritation and redness develop

Keep out of reach of children.

if swallowed, get medical help or contact a Poison Control Center right away

Directions

- wet hands thoroughly with product and allow to dry without wiping

Other information

- Store at 68F to 77F (20C - 25C)
- Do not store above 110F (43C)
- You may report a serious adverse reaction to this product to Report Reaction, LLC, PO Box 22, Plainsboro, NJ 08536

Inactive ingredients

Water, Glycerin, Propylene Glycol, Carbomer, Aloe Barbadensis Leaf Extract, Aminomethyl Propanol, Fragrance, Tocopheryl Acetate, Denatonium Benzoate, Yellow 5, Blue 1.

Company Information

MANUFACTURED FOR & DIST. BY K7 DESIGN GROUP LLC

2433 KNAPP ST. BROOKLYN, NY 11235